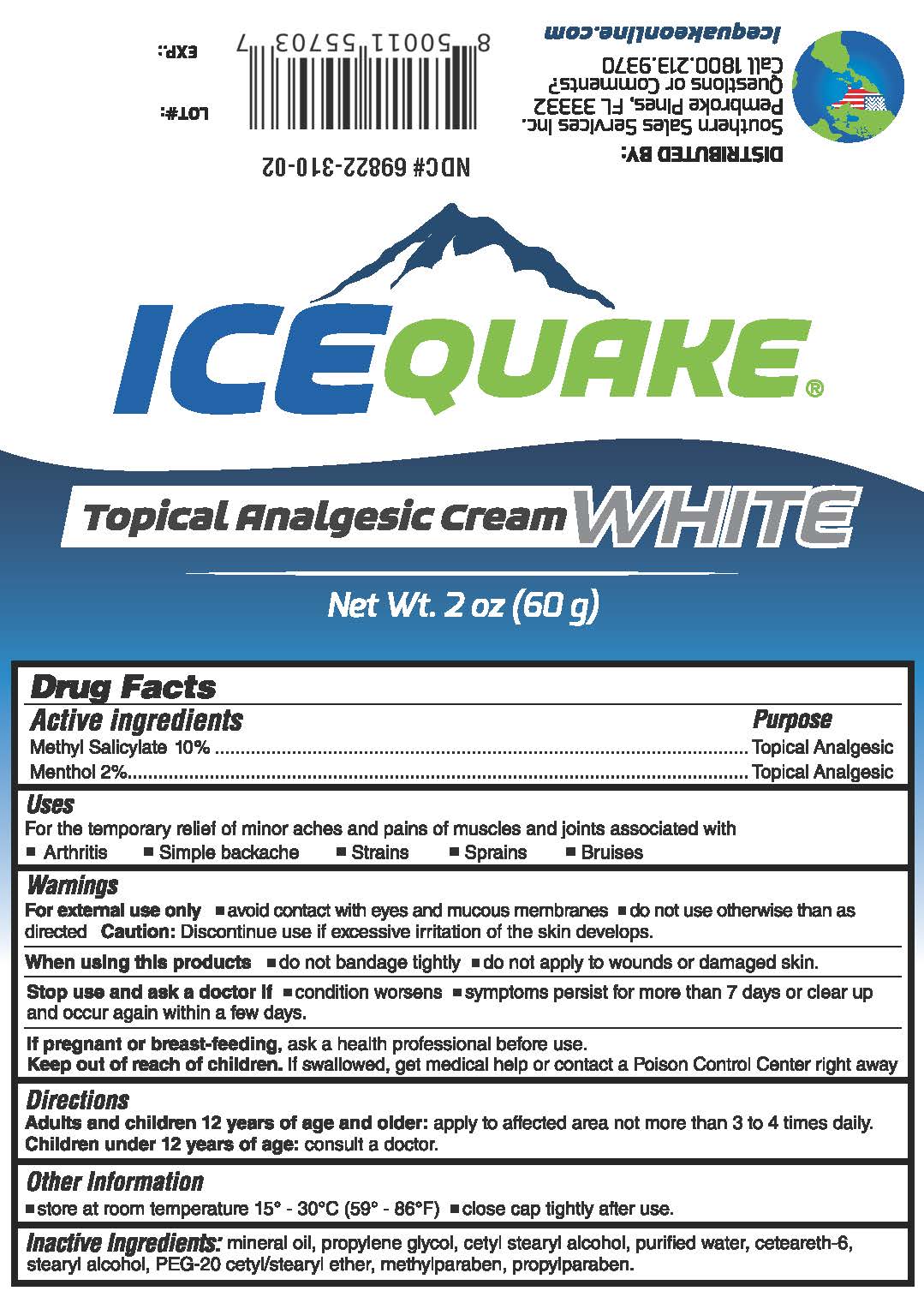 DRUG LABEL: IceQuake Analgestic White
NDC: 69822-310 | Form: CREAM
Manufacturer: Southern Sales & Service, Inc.
Category: otc | Type: HUMAN OTC DRUG LABEL
Date: 20231129

ACTIVE INGREDIENTS: METHYL SALICYLATE 10 g/100 g; MENTHOL 2 g/100 g
INACTIVE INGREDIENTS: MINERAL OIL; PROPYLENE GLYCOL; CETOSTEARYL ALCOHOL; WATER; CETEARETH-6; STEARYL ALCOHOL; POLYOXYL 20 CETOSTEARYL ETHER; METHYLPARABEN; PROPYLPARABEN

IceQuake Analgestic White

Active ingredients

Menthyl Salicylate 10%

Menthol 2%

Purpose

Topical Analgesic

Topical Analgesic

Uses

For temporary relief of minor aches and pains of muscles and joints associated with

- Arthritis
- Simple backache
- Strains
- Sprains
- Bruises

Warnings

For external use only

Discontinue use if excessive irritation of the skin develops. Caution:

- avoid contact with eyes and mucous membranes
- do not use otherwise than as directed

When using this products

- do not bandage tightly
- do not apply to wounds or damaged skin.

Stop use and ask a doctor if

- condition worsens
- symptoms persist for more than 7 days or clear up and occur again within a few days.

If pregnant or breast-feeding,

ask a health professional before use.

Keep out of reach of children.

If swallowed, get medical help or contact a Poison Control Center right away

Directions

apply to affected area not more than 3 to 4 times daily. Audlts and children 12 years of age and older:

: consult a doctor. Children under 12 years of age

Other Information

store at room temperature 15° - 30°C (59° - 86°F)

close cap tightly after use.

Inactive Ingredients

mineral oil, propylene gylcol, cetyl stearyl alcohol, purified water, ceteareth-6, stearyl alcohol, PEG-20 cetyl/stearyl ether, methylparaben, propylparaben.